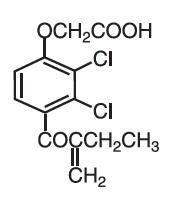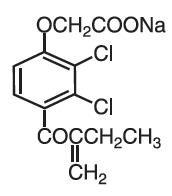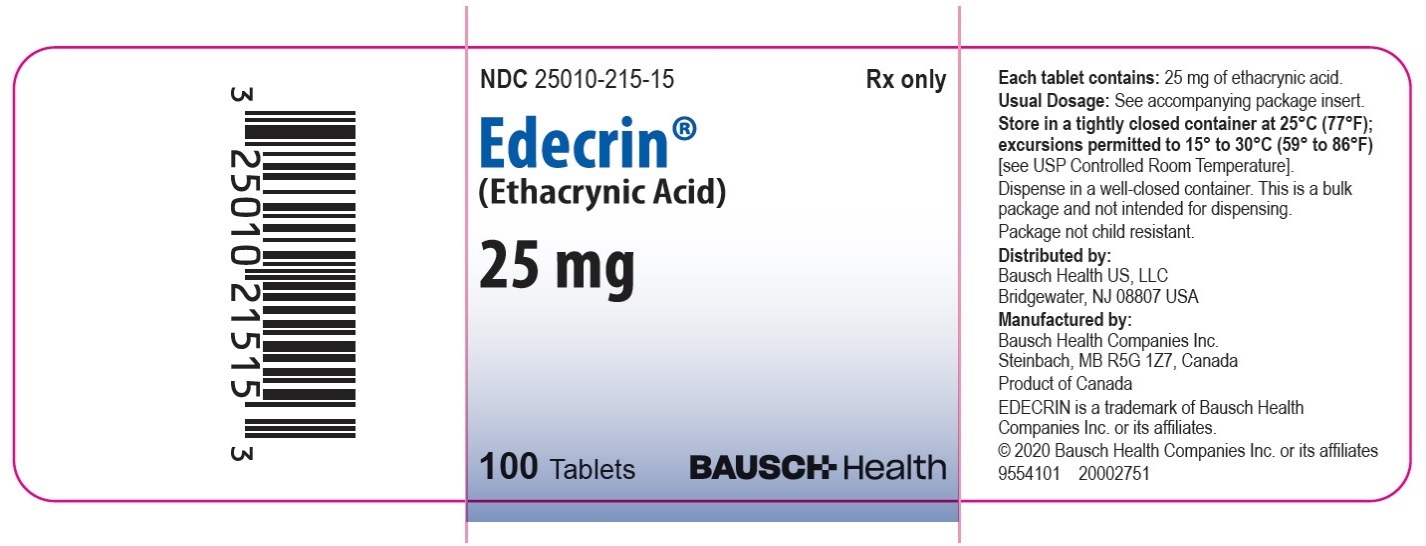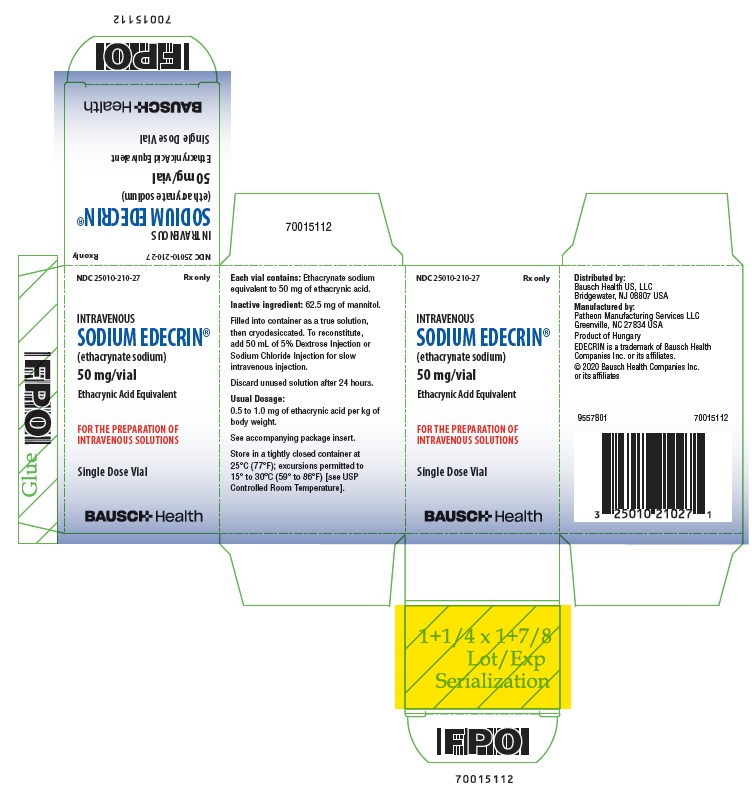 DRUG LABEL: EDECRIN
NDC: 25010-215 | Form: TABLET
Manufacturer: Bausch Health US, LLC
Category: prescription | Type: HUMAN PRESCRIPTION DRUG LABEL
Date: 20200831

ACTIVE INGREDIENTS: ethacrynic acid 25 mg/1 1
INACTIVE INGREDIENTS: Silicon Dioxide; Magnesium Stearate; Talc; LACTOSE, UNSPECIFIED FORM

TABLETS
EDECRIN®
(ethacrynic acid)
and
INTRAVENOUS
SODIUM EDECRIN®
(ethacrynate sodium)

EDECRIN (ethacrynic acid) is a potent diuretic which, if given in excessive amounts, may lead to profound diuresis with water and electrolyte depletion. Therefore, careful medical supervision is required, and dose and dose schedule must be adjusted to the individual patient’s needs (see DOSAGE AND ADMINISTRATION).

DESCRIPTION

Ethacrynic acid is an unsaturated ketone derivative of an aryloxyacetic acid. It is designated chemically as [2,3-dichloro-4-(2-methylene-1-oxobutyl)phenoxy] acetic acid, and has a molecular weight of 303.14. Ethacrynic acid is a white, or practically white, crystalline powder, very slightly soluble in water, but soluble in most organic solvents such as alcohols, chloroform, and benzene. Its empirical formula is C13H12Cl2O4 and its structural formula is:

Ethacrynate sodium, the sodium salt of ethacrynic acid, is soluble in water at 25°C to the extent of about 7 percent. Solutions of the sodium salt are relatively stable at about pH 7 at room temperature for short periods, but as the pH or temperature increases the solutions are less stable. The molecular weight of ethacrynate sodium is 325.12. Its empirical formula is C13H11Cl2NaO4 and its structural formula is:

EDECRIN is supplied as 25 mg tablets for oral use. The tablets contain the following inactive ingredients: colloidal silicon dioxide, lactose, magnesium stearate, starch and talc. Intravenous SODIUM EDECRIN (ethacrynate sodium) is a sterile freeze-dried powder and is supplied in a vial containing:

Ethacrynate sodium equivalent to ethacrynic acid……. 50.0 mg

Inactive ingredient:

Mannitol…………….62.5 mg

CLINICAL PHARMACOLOGY

Pharmacokinetics and Metabolism

EDECRIN acts on the ascending limb of the loop of Henle and on the proximal and distal tubules. Urinary output is usually dose dependent and related to the magnitude of fluid accumulation. Water and electrolyte excretion may be increased several times over that observed with thiazide diuretics, since EDECRIN inhibits reabsorption of a much greater proportion of filtered sodium than most other diuretic agents. Therefore, EDECRIN is effective in many patients who have significant degrees of renal insufficiency (see WARNINGS concerning deafness). EDECRIN has little or no effect on glomerular filtration or on renal blood flow, except following pronounced reductions in plasma volume when associated with rapid diuresis.

The electrolyte excretion pattern of ethacrynic acid varies from that of the thiazides and mercurial diuretics. Initial sodium and chloride excretion is usually substantial and chloride loss exceeds that of sodium. With prolonged administration, chloride excretion declines, and potassium and hydrogen ion excretion may increase. EDECRIN is effective whether or not there is clinical acidosis or alkalosis.

Although EDECRIN, in carefully controlled studies in animals and experimental subjects, produces a more favorable sodium/potassium excretion ratio than the thiazides, in patients with increased diuresis excessive amounts of potassium may be excreted.

Onset of action is rapid, usually within 30 minutes after an oral dose of EDECRIN or within 5 minutes after an intravenous injection of SODIUM EDECRIN. After oral use, diuresis peaks in about 2 hours and lasts about 6 to 8 hours.

The sulfhydryl binding propensity of ethacrynic acid differs somewhat from that of the organomercurials. Its mode of action is not by carbonic anhydrase inhibition.

Ethacrynic acid does not cross the blood-brain barrier.

INDICATIONS AND USAGE

EDECRIN is indicated for treatment of edema when an agent with greater diuretic potential than those commonly employed is required.

1. Treatment of the edema associated with congestive heart failure, cirrhosis of the liver, and renal disease, including the nephrotic syndrome.
2. Short-term management of ascites due to malignancy, idiopathic edema, and lymphedema.
3. Short-term management of hospitalized pediatric patients, other than infants, with congenital heart disease or the nephrotic syndrome.
4. Intravenous SODIUM EDECRIN is indicated when a rapid onset of diuresis is desired, e.g., in acute pulmonary edema, or when gastrointestinal absorption is impaired or oral medication is not practicable.

CONTRAINDICATIONS

All diuretics, including ethacrynic acid, are contraindicated in anuria. If increasing electrolyte imbalance, azotemia, and/or oliguria occur during treatment of severe, progressive renal disease, the diuretic should be discontinued.

In a few patients this diuretic has produced severe, watery diarrhea. If this occurs, it should be discontinued and not used again.

Until further experience in infants is accumulated, therapy with oral and parenteral EDECRIN is contraindicated.

Hypersensitivity to any component of this product.

WARNINGS

The effects of EDECRIN on electrolytes are related to its renal pharmacologic activity and are dose dependent. The possibility of profound electrolyte and water loss may be avoided by weighing the patient throughout the treatment period, by careful adjustment of dosage, by initiating treatment with small doses, and by using the drug on an intermittent schedule when possible. When excessive diuresis occurs, the drug should be withdrawn until homeostasis is restored. When excessive electrolyte loss occurs, the dosage should be reduced or the drug temporarily withdrawn.

Initiation of diuretic therapy with EDECRIN in the cirrhotic patient with ascites is best carried out in the hospital. When maintenance therapy has been established, the individual can be satisfactorily followed as an outpatient. EDECRIN should be given with caution to patients with advanced cirrhosis of the liver, particularly those with a history of previous episodes of electrolyte imbalance or hepatic encephalopathy. Like other diuretics it may precipitate hepatic coma and death.

Too vigorous a diuresis, as evidenced by rapid and excessive weight loss, may induce an acute hypotensive episode. In elderly cardiac patients, rapid contraction of plasma volume and the resultant hemoconcentration should be avoided to prevent the development of thromboembolic episodes, such as cerebral vascular thromboses and pulmonary emboli which may be fatal. Excessive loss of potassium in patients receiving digitalis glycosides may precipitate digitalis toxicity. Care should also be exercised in patients receiving potassium-depleting steroids.

A number of possibly drug-related deaths have occurred in critically ill patients refractory to other diuretics. These generally have fallen into two categories: (1) patients with severe myocardial disease who have been receiving digitalis and presumably developed acute hypokalemia with fatal arrhythmia; (2) patients with severely decompensated hepatic cirrhosis with ascites, with or without accompanying encephalopathy, who were in electrolyte imbalance and died because of intensification of the electrolyte defect.

Deafness, tinnitus, and vertigo with a sense of fullness in the ears have occurred, most frequently in patients with severe impairment of renal function. These symptoms have been associated most often with intravenous administration and with doses in excess of those recommended. The deafness has usually been reversible and of short duration (one to 24 hours). However, in some patients the hearing loss has been permanent. A number of these patients were also receiving drugs known to be ototoxic. EDECRIN may increase the ototoxic potential of other drugs (see PRECAUTIONS, Drug Interactions).

Lithium generally should not be given with diuretics (see PRECAUTIONS, Drug Interactions).

PRECAUTIONS

General

Weakness, muscle cramps, paresthesias, thirst, anorexia, and signs of hyponatremia, hypokalemia, and/or hypochloremic alkalosis may occur following vigorous or excessive diuresis and these may be accentuated by rigid salt restriction. Rarely, tetany has been reported following vigorous diuresis. During therapy with ethacrynic acid, liberalization of salt intake and supplementary potassium chloride are often necessary.

When a metabolic alkalosis may be anticipated, e.g., in cirrhosis with ascites, the use of potassium chloride or a potassium-sparing agent before and during therapy with EDECRIN may mitigate or prevent the hypokalemia.

Loop diuretics have been shown to increase the urinary excretion of magnesium; this may result in hypomagnesemia.

The safety and efficacy of ethacrynic acid in hypertension have not been established. However, the dosage of coadministered antihypertensive agents may require adjustment.

Orthostatic hypotension may occur in patients receiving other antihypertensive agents when given ethacrynic acid.

EDECRIN has little or no effect on glomerular filtration or on renal blood flow, except following pronounced reductions in plasma volume when associated with rapid diuresis. A transient increase in serum urea nitrogen may occur. Usually, this is readily reversible when the drug is discontinued.

As with other diuretics used in the treatment of renal edema, hypoproteinemia may reduce responsiveness to ethacrynic acid and the use of salt-poor albumin should be considered.

A number of drugs, including ethacrynic acid, have been shown to displace warfarin from plasma protein; a reduction in the usual anticoagulant dosage may be required in patients receiving both drugs.

EDECRIN may increase the risk of gastric hemorrhage associated with corticosteroid treatment.

Laboratory Tests

Frequent serum electrolyte, CO2 and BUN determinations should be performed early in therapy and periodically thereafter during active diuresis. Any electrolyte abnormalities should be corrected or the drug temporarily withdrawn.

Increases in blood glucose and alterations in glucose tolerance tests have been observed in patients receiving EDECRIN.

Drug Interactions

Lithium generally should not be given with diuretics because they reduce its renal clearance and add a high risk of lithium toxicity. Read circulars for lithium preparations before use of such concomitant therapy.

EDECRIN may increase the ototoxic potential of other drugs such as aminoglycoside and some cephalosporin antibiotics. Their concurrent use should be avoided.

A number of drugs, including ethacrynic acid, have been shown to displace warfarin from plasma protein; a reduction in the usual anticoagulant dosage may be required in patients receiving both drugs.

In some patients, the administration of a non-steroidal anti-inflammatory agent can reduce the diuretic, natriuretic, and antihypertensive effects of loop, potassium-sparing and thiazide diuretics. Therefore, when EDECRIN and non-steroidal anti-inflammatory agents are used concomitantly, the patient should be observed closely to determine if the desired effect of the diuretic is obtained.

Carcinogenesis, Mutagenesis, Impairment of Fertility

There was no evidence of a tumorigenic effect in a 79-week oral chronic toxicity study in rats at doses up to 45 times the human dose.

Ethacrynic acid had no effect on fertility in a two-litter study in rats or a two-generation study in mice at 10 times the human dose.

Pregnancy

Reproduction studies in the mouse and rabbit at doses up to 50 times the human dose showed no evidence of external abnormalities of the fetus due to EDECRIN.

In a two-litter study in the dog and rat, oral doses of 5 or 20 mg/kg/day (2½ or 10 times the human dose), respectively, did not interfere with pregnancy or with growth and development of the pups. Although there was reduction in the mean body weights of the fetuses in a teratogenic study in the rat at a dose level of 100 mg/kg (50 times the human dose), there was no effect on mortality or postnatal development. Functional and morphologic abnormalities were not observed.

There are, however, no adequate and well-controlled studies in pregnant women. Since animal reproduction studies are not always predictive of human response, EDECRIN should be used during pregnancy only if clearly needed.

Nursing Mothers

It is not known whether this drug is excreted in human milk. Because many drugs are excreted in human milk and because of the potential for serious adverse reactions in nursing infants from EDECRIN, a decision should be made whether to discontinue nursing or to discontinue the drug, taking into account the importance of the drug to the mother.

Pediatric Use

There are no well-controlled clinical trials in pediatric patients. The information on oral dosing in pediatric patients, other than infants, is supported by evidence from empiric use in this age group.

For information on oral use in pediatric patients, other than infants, see INDICATIONS AND USAGE and DOSAGE AND ADMINISTRATION.

Safety and effectiveness of oral and parenteral use in infants have not been established (see CONTRAINDICATIONS).

Safety and effectiveness of intravenous use in pediatric patients have not been established (see DOSAGE AND ADMINISTRATION, Intravenous Use).

Geriatric Use

Of the total number of subjects in clinical studies of EDECRIN/SODIUM EDECRIN, approximately 224 patients (21%) were 65 to 74 years of age, while approximately 100 patients (9%) were 75 years of age and over. No overall differences in safety or effectiveness were observed between these subjects and younger subjects, and other reported clinical experience has not identified differences in responses between the elderly and younger patients, but greater sensitivity of some older individuals cannot be ruled out. (See WARNINGS.)

This drug is known to be substantially excreted by the kidney, and the risk of toxic reactions to this drug may be greater in patients with impaired renal function. Because elderly patients are more likely to have decreased renal function, care should be taken in dose selection, and it may be useful to monitor renal function. (See CONTRAINDICATIONS.)

ADVERSE REACTIONS

Gastrointestinal

Anorexia, malaise, abdominal discomfort or pain, dysphagia, nausea, vomiting, and diarrhea have occurred. These are more frequent with large doses or after one to three months of continuous therapy. A few patients have had sudden onset of profuse, watery diarrhea. Discontinue EDECRIN if diarrhea is severe and do not give it again. Gastrointestinal bleeding has occurred in some patients. Rarely, acute pancreatitis has been reported.

Metabolic

Reversible hyperuricemia and acute gout have been reported. Acute symptomatic hypoglycemia with convulsions occurred in two uremic patients who received doses above those recommended. Hyperglycemia has been reported. Rarely, jaundice and abnormal liver function tests have been reported in seriously ill patients receiving multiple drug therapy, including EDECRIN.

Hematologic

Agranulocytosis or severe neutropenia has been reported in a few critically ill patients also receiving agents known to produce this effect. Thrombocytopenia has been reported rarely. Henoch-Schönlein purpura has been reported rarely in patients with rheumatic heart disease receiving multiple drug therapy, including EDECRIN.

Special Senses

(see WARNINGS)

Deafness, tinnitus and vertigo with a sense of fullness in the ears, and blurred vision have occurred.

Central Nervous System

Headache, fatigue, apprehension, confusion.

Miscellaneous

Skin rash, fever, chills, hematuria.

SODIUM EDECRIN occasionally has caused local irritation and pain after intravenous use.

To report SUSPECTED ADVERSE REACTIONS, contact Bausch Health US, LLC at 1-800-321-4576 or FDA at 1-800-FDA-1088 or www.fda.gov/medwatch.

OVERDOSAGE

Overdosage may lead to excessive diuresis with electrolyte depletion and dehydration.

In the event of overdosage, symptomatic and supportive measures should be employed. Emesis should be induced or gastric lavage performed. Correct dehydration, electrolyte imbalance, hepatic coma, and hypotension by established procedures. If required, give oxygen or artificial respiration for respiratory impairment.

In the mouse, the oral LD50 of ethacrynic acid is 627 mg/kg and the intravenous LD50 of ethacrynate sodium is 175 mg/kg.

DOSAGE AND ADMINISTRATION

Dosage must be regulated carefully to prevent a more rapid or substantial loss of fluid or electrolyte than is indicated or necessary. The magnitude of diuresis and natriuresis is largely dependent on the degree of fluid accumulation present in the patient. Similarly, the extent of potassium excretion is determined in large measure by the presence and magnitude of aldosteronism.

Oral Use

EDECRIN is available for oral use as 25 mg tablets.

In Adults:

The smallest dose required to produce gradual weight loss (about 1 to 2 pounds per day) is recommended. Onset of diuresis usually occurs at 50 to 100 mg for adults. After diuresis has been achieved, the minimally effective dose (usually from 50 to 200 mg daily) may be given on a continuous or intermittent dosage schedule. Dosage adjustments are usually in 25 to 50 mg increments to avoid derangement of water and electrolyte excretion.

The patient should be weighed under standard conditions before and during the institution of diuretic therapy with this compound. Small alterations in dose should effectively prevent a massive diuretic response. The following schedule may be helpful in determining the smallest effective dose.

Day 1 — 50 mg once daily after a meal
Day 2 — 50 mg twice daily after meals, if necessary
Day 3 — 100 mg in the morning and 50 to 100 mg following the afternoon or evening meal, depending upon response to the morning dose.

A few patients may require initial and maintenance doses as high as 200 mg twice daily. These higher doses, which should be achieved gradually, are most often required in patients with severe, refractory edema.

In Pediatric Patients

(excluding infants, see CONTRAINDICATIONS): The initial dose should be 25 mg. Careful stepwise increments in dosage of 25 mg should be made to achieve effective maintenance.

Maintenance Therapy

It is usually possible to reduce the dosage and frequency of administration once dry weight has been achieved.

EDECRIN (Ethacrynic Acid) may be given intermittently after an effective diuresis is obtained with the regimen outlined above. Dosage may be on an alternate daily schedule or more prolonged periods of diuretic therapy may be interspersed with rest periods. Such an intermittent dosage schedule allows time for correction of any electrolyte imbalance and may provide a more efficient diuretic response.

The chloruretic effect of this agent may give rise to retention of bicarbonate and a metabolic alkalosis. This may be corrected by giving chloride (ammonium chloride or arginine chloride). Ammonium chloride should not be given to cirrhotic patients.

EDECRIN has additive effects when used with other diuretics. For example, a patient who is on maintenance dosage of an oral diuretic may require additional intermittent diuretic therapy, such as an organomercurial, for the maintenance of basal weight. The intermittent use of EDECRIN orally may eliminate the need for injections of organomercurials. Small doses of EDECRIN may be added to existing diuretic regimens to maintain basal weight. This drug may potentiate the action of carbonic anhydrase inhibitors, with augmentation of natriuresis and kaliuresis. Therefore, when adding EDECRIN the initial dose and changes of dose should be in 25 mg increments, to avoid electrolyte depletion. Rarely, patients who failed to respond to ethacrynic acid have responded to older established agents.

While many patients do not require supplemental potassium, the use of potassium chloride or potassium-sparing agents, or both, during treatment with EDECRIN is advisable, especially in cirrhotic or nephrotic patients and in patients receiving digitalis.

Salt liberalization usually prevents the development of hyponatremia and hypochloremia. During treatment with EDECRIN, salt may be liberalized to a greater extent than with other diuretics. Cirrhotic patients, however, usually require at least moderate salt restriction concomitant with diuretic therapy.

Intravenous Use

Intravenous SODIUM EDECRIN is for intravenous use when oral intake is impractical or in urgent conditions, such as acute pulmonary edema.

The usual intravenous dose for the average sized adult is 50 mg, or 0.5 to 1.0 mg per kg of body weight. Usually only one dose has been necessary; occasionally a second dose at a new injection site, to avoid possible thrombophlebitis, may be required. A single intravenous dose not exceeding 100 mg has been used in critical situations.

Insufficient pediatric experience precludes recommendation for this age group.

To reconstitute the dry material, add 50 mL of 5% Dextrose Injection, or Sodium Chloride Injection to the vial. Occasionally, some 5% Dextrose Injection solutions may have a low pH (below 5). The resulting solution with such a diluent may be hazy or opalescent. Intravenous use of such a solution is not recommended. Inspect the vial containing intravenous SODIUM EDECRIN for particulate matter and discoloration before use.

The solution may be given slowly through the tubing of a running infusion or by direct intravenous injection over a period of several minutes. Do not mix this solution with whole blood or its derivatives. Discard unused reconstituted solution after 24 hours.

SODIUM EDECRIN should not be given subcutaneously or intramuscularly because of local pain and irritation.

HOW SUPPLIED

Tablets EDECRIN, 25 mg, are white, capsule shaped, scored tablets, coded VRX 205 on one side and EDECRIN on the other. They are supplied as follows:

NDC 25010-215-15 in bottles of 100.

Intravenous SODIUM EDECRIN is a dry white material either in a plug form or as a powder. It is supplied in vials containing ethacrynate sodium equivalent to 50 mg of ethacrynic acid.

NDC 25010-210-27

Storage

Store in a tightly closed container at 25°C (77°F); excursions permitted to 15° to 30°C (59° to 86°F) [see USP Controlled Room Temperature].

EDECRIN® Tablets (ethacrynic acid)
Distributed by:
Bausch Health US, LLC
Bridgewater, NJ 08807 USA
Manufactured by:
Bausch Health Companies Inc.
Steinbach, MB R5G 1Z7, Canada

SODIUM EDECRIN® Intravenous (ethacrynate sodium)
Distributed by:
Bausch Health US, LLC
Bridgewater, NJ 08807 USA
Manufactured by:
Patheon Manufacturing Services LLC
Greenville, NC 27834 USA

EDECRIN is a trademark of Bausch Health Companies Inc. or its affiliates.

© 2020 Bausch Health Companies Inc. or its affiliates

Rev. 08/2020

9550601 70015111

PRINCIPAL DISPLAY PANEL - 25 mg Bottle Label

NDC 25010-215-15

Rx only

Edecrin®
(Ethacrynic Acid)

25 mg

100 Tablets

BAUSCH Health

Package/Label Display Panel – 50 mg vial

NDC 25010-210-27

Rx only

INTRAVENOUS
SODIUM EDECRIN®
(ethacrynate sodium)

50 mg/vial

Ethacrynic Acid Equivalent

FOR THE PREPARATION OF
INTRAVENOUS SOLUTIONS

Single Dose Vial

BAUSCH Health